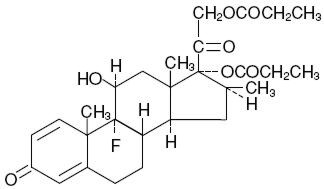 DRUG LABEL: Unknown
Manufacturer: Warrick Pharmaceuticals Corporation
Category: prescription | Type: HUMAN PRESCRIPTION DRUG LABELING
Date: 20061207

Augmented Betamethasone Dipropionate [Vehicle augments the penetration of the steroid.]
Ointment 0.05%
(potency expressed as betamethasone)

For Dermatologic Use Only– Not for Ophthalmic Use

PRODUCT INFORMATION

DESCRIPTION

Augmented Betamethasone Dipropionate Ointment contains betamethasone dipropionate, USP, a synthetic adrenocorticosteroid, for dermatologic use. Betamethasone, an analog of prednisolone, has a high degree of corticosteroid activity and a slight degree of mineralocorticoid activity. Betamethasone dipropionate is the 17,21-dipropionate ester of betamethasone.

Chemically, betamethasone dipropionate is 9-fluoro-11β, 17,21-trihydroxy-16β-methyl-pregna-1,4-diene-3,20-dione 17,21-dipropionate, with the empirical formula C28H37FO7, a molecular weight of 504.6, and the following structural formula:

Betamethasone dipropionate is a white to creamy white, odorless crystalline powder, insoluble in water.

Each gram of Augmented Betamethasone Dipropionate Ointment 0.05% contains: 0.643 mg betamethasone dipropionate, USP (equivalent to 0.5 mg betamethasone), in ACTIBASE®, an optimized vehicle of propylene glycol; propylene glycol stearate (55% monoester); white wax; and white petrolatum.

CLINICAL PHARMACOLOGY

The corticosteroids are a class of compounds comprising steroid hormones secreted by the adrenal cortex and their synthetic analogs. In pharmacologic doses, corticosteroids are used primarily for their anti-inflammatory and/or immunosuppressive effects.

Topical corticosteroids, such as betamethasone dipropionate, are effective in the treatment of corticosteroid-responsive dermatoses primarily because of their anti-inflammatory, antipruritic, and vasoconstrictive actions. However, while the physiologic, pharmacologic, and clinical effects of the corticosteroids are well known, the exact mechanisms of their actions in each disease are uncertain. Betamethasone dipropionate, a corticosteroid, has been shown to have topical (dermatologic) and systemic pharmacologic and metabolic effects characteristic of this class of drugs.

Pharmacokinetics

The extent of percutaneous absorption of topical corticosteroids is determined by many factors including the vehicle, the integrity of the epidermal barrier, and the use of occlusive dressings. (See DOSAGE AND ADMINISTRATION section.)

Topical corticosteroids can be absorbed from normal intact skin. Inflammation and/or other disease processes in the skin may increase percutaneous absorption. Occlusive dressings substantially increase the percutaneous absorption of topical corticosteroids. (See DOSAGE AND ADMINISTRATION section.)

Once absorbed through the skin, topical corticosteroids enter pharmacokinetic pathways similar to systemically administered corticosteroids. Corticosteroids are bound to plasma proteins in varying degrees. Corticosteroids are metabolized primarily in the liver and are then excreted by the kidneys. Some of the topical corticosteroids and their metabolites are also excreted into the bile.

At 14 g per day, Augmented Betamethasone Dipropionate Ointment was shown to depress the plasma levels of adrenal cortical hormones following repeated application to diseased skin in patients with psoriasis. Adrenal depression in these patients was transient, and rapidly returned to normal upon cessation of treatment. At 7 g per day (3.5 g b.i.d.), Augmented Betamethasone Dipropionate Ointment was shown to cause minimal inhibition of the hypothalamic-pituitary-adrenal (HPA) axis when applied two times daily for 2 to 3 weeks, in normal patients and in patients with psoriasis and eczematous disorders.

With 6 g to 7 g of Augmented Betamethasone Dipropionate Ointment applied once daily for 3 weeks, no significant inhibition of the HPA axis was observed in patients with psoriasis and atopic dermatitis, as measured by plasma cortisol and 24-hour urinary 17-hydroxy-corticosteroid levels.

INDICATIONS AND USAGE

Augmented Betamethasone Dipropionate Ointment is indicated for relief of the inflammatory and pruritic manifestations of corticosteroid-responsive dermatoses.

CONTRAINDICATIONS

Augmented Betamethasone Dipropionate Ointment is contraindicated in patients who are hypersensitive to betamethasone dipropionate, to other corticosteroids, or to any ingredient in this preparation.

PRECAUTIONS

General

Systemic absorption of topical corticosteroids has produced reversible HPA axis suppression, manifestations of Cushing's syndrome, hyperglycemia, and glucosuria in some patients.

Conditions which augment systemic absorption include the application of the more potent corticosteroids, use over large surface areas, prolonged use, and the addition of occlusive dressings. (See DOSAGE AND ADMINISTRATION section.)

Therefore, patients receiving a large dose of a potent topical steroid applied to a large surface area should be evaluated periodically for evidence of HPA axis suppression by using the urinary free cortisol and ACTH stimulation tests. If HPA axis suppression is noted, an attempt should be made to withdraw the drug, reduce the frequency of application, or substitute a less potent steroid.

Recovery of HPA axis function is generally prompt and complete upon discontinuation of the drug. Infrequently, signs and symptoms of steroid withdrawal may occur, requiring supplemental systemic corticosteroids.

Children may absorb proportionally larger amounts of topical corticosteroids and thus be more susceptible to systemic toxicity. (See PRECAUTIONS–Pediatric Use.)

If irritation develops, topical corticosteroids should be discontinued and appropriate therapy instituted.

In the presence of dermatological infections, the use of an appropriate antifungal or antibacterial agent should be instituted. If a favorable response does not occur promptly, the corticosteroid should be discontinued until the infection has been adequately controlled.

Information for Patients

Patients using topical corticosteroids should receive the following information and instructions:

1. This medication is to be used as directed by the physician and should not be used longer than the prescribed time period. It is for external use only. Avoid contact with the eyes.
2. Patients should be advised not to use this medication for any disorder other than that for which it was prescribed.
3. The treated skin area should not be bandaged or otherwise covered or wrapped as to be occlusive. (See DOSAGE AND ADMINISTRATION section.)
4. Patients should report any signs of local adverse reactions.

Laboratory Tests

The following tests may be helpful in evaluating HPA axis suppression:

Urinary free cortisol test
ACTH stimulation test

Carcinogenesis, Mutagenesis, and Impairment of Fertility

Long-term animal studies have not been performed to evaluate the carcinogenic potential or the effect on fertility of topically applied corticosteroids.

Studies to determine mutagenicity with prednisolone have revealed negative results.

Pregnancy Category C

Corticosteroids are generally teratogenic in laboratory animals when administered systemically at relatively low dosage levels. The more potent corticosteroids have been shown to be teratogenic after dermal application in laboratory animals. There are no adequate and well-controlled studies of the teratogenic effects of topically applied corticosteroids in pregnant women. Therefore, topical corticosteroids should be used during pregnancy only if the potential benefit justifies the potential risk to the fetus. Drugs of this class should not be used extensively on pregnant patients, in large amounts, or for prolonged periods of time.

Nursing Mothers

It is not known whether topical administration of corticosteroids could result in sufficient systemic absorption to produce detectable quantities in breast milk. Systemically administered corticosteroids are secreted into breast milk in quantities not likely to have a deleterious effect on the infant. Nevertheless, caution should be exercised when topical corticosteroids are prescribed for a nursing woman.

Pediatric Use

Data regarding use of Augmented Betamethasone Dipropionate Ointment in pediatric patients are not available, so use of this product in patients under the age of 12 is not recommended.

Pediatric patients may demonstrate greater susceptibility to topical corticosteroid-induced HPA axis suppression and Cushing's syndrome than mature patients because of a larger skin surface area to body weight ratio.

Hypothalamic-pituitary-adrenal (HPA) axis suppression, Cushing's syndrome, and intracranial hypertension have been reported in children receiving topical corticosteroids. Manifestations of adrenal suppression in children include linear growth retardation, delayed weight gain, low plasma cortisol levels, and absence of response to ACTH stimulation. Manifestations of intracranial hypertension include bulging fontanelles, headaches, and bilateral papilledema.

Administration of topical corticosteroids to children should be limited to the least amount compatible with an effective therapeutic regimen. Chronic corticosteroid therapy may interfere with the growth and development of children.

ADVERSE REACTIONS

The local adverse reactions reported with Augmented Betamethasone Dipropionate Ointment applied either once or twice a day during clinical studies are as follows: erythema, 3 per 767 patients; folliculitis, 2 per 767 patients; pruritus, 2 per 767 patients; vesiculation, 1 per 767 patients.

The following local adverse reactions are reported infrequently when topical corticosteroids are used as recommended. These reactions are listed in an approximate decreasing order of occurrence: burning, itching, irritation, dryness, folliculitis, hypertrichosis, acneiform eruptions, hypopigmentation, perioral dermatitis, allergic contact dermatitis, maceration of the skin, secondary infection, skin atrophy, striae, miliaria.

Systemic absorption of topical corticosteroids has produced reversible HPA axis suppression, manifestations of Cushing's syndrome, hyperglycemia, and glucosuria in some patients.

OVERDOSAGE

Topically applied corticosteroids can be absorbed in sufficient amounts to produce systemic effects. (See PRECAUTIONS.)

DOSAGE AND ADMINISTRATION

Apply a thin film of Augmented Betamethasone Dipropionate Ointment to the affected skin areas once or twice daily. Treatment with Augmented Betamethasone Dipropionate Ointment should be limited to 45 g per week.

Augmented Betamethasone Dipropionate Ointment is not to be used with occlusive dressings.

HOW SUPPLIED

Augmented Betamethasone Dipropionate Ointment 0.05% is supplied in 15-g (NDC 59930-1575-1) and 50-g (NDC 59930-1575-3) tubes; boxes of one.

Store at 25°C (77°F); excursions permitted to 15–30°C (59–86°F) [see USP Controlled Room Temperature]

Warrick Pharmaceuticals Corporation
Reno, NV 89506 USA

Rev. 3/04
28362102

Copyright © 1995, 1996, 1999, Warrick Pharmaceuticals Corporation.
All rights reserved.